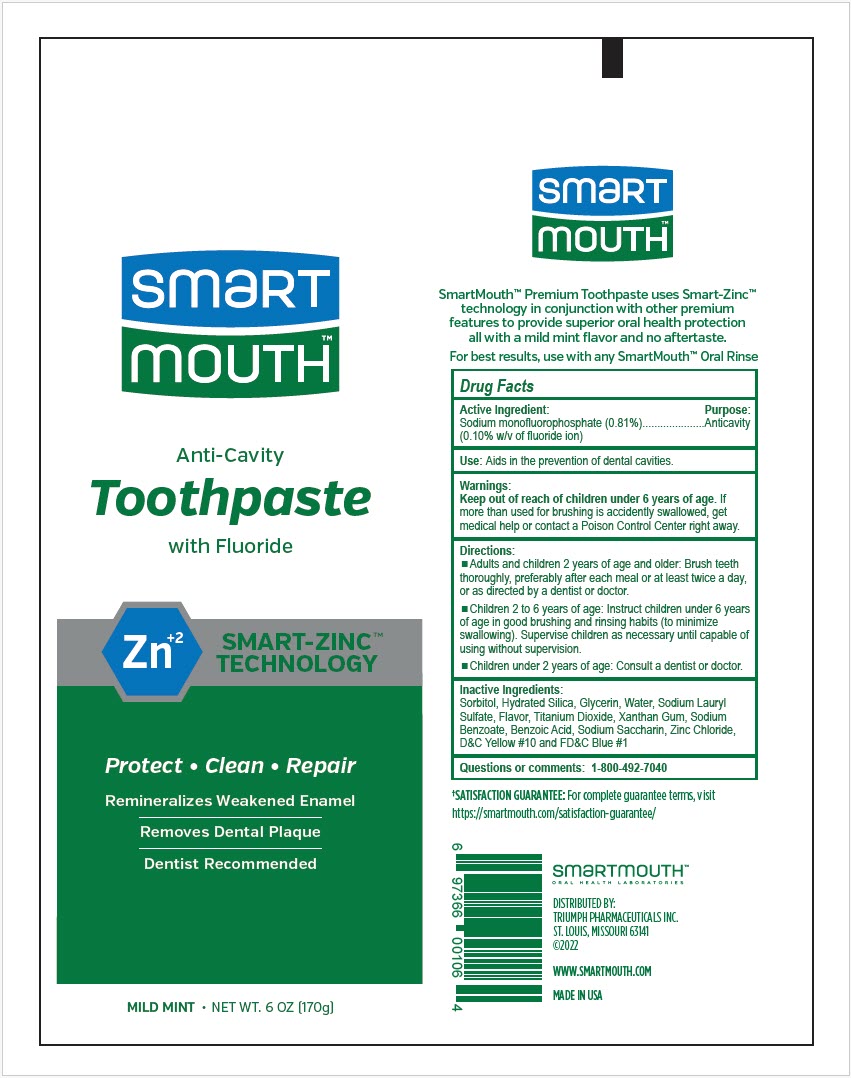 DRUG LABEL: SmartMouth 
NDC: 76357-106 | Form: PASTE, DENTIFRICE
Manufacturer: Triumph Pharmaceuticals Inc.
Category: otc | Type: HUMAN OTC DRUG LABEL
Date: 20241230

ACTIVE INGREDIENTS: Sodium Monofluorophosphate 1 mg/1 g
INACTIVE INGREDIENTS: Sorbitol; Hydrated Silica; Glycerin; Water; Sodium Lauryl Sulfate; Titanium Dioxide; Xanthan Gum; Sodium Benzoate; Benzoic Acid; Saccharin Sodium; Zinc Chloride; D&C Yellow No. 10; FD&C Blue No. 1

Smart
Mouth™
ADVANCED
CLINICAL FORMULA™
TOOTHPASTE

Drug Facts

Active Ingredient

Sodium monofluorophosphate (0.81%) (0.10% w/v of fluoride ion)

Purpose

Anticavity

Use

- Aids in the prevention of dental cavities.

Warnings

Keep out of reach of children under 6 years of age. If more than used for brushing is accidently swallowed, get medical help or contact a Poison Control Center right away.

Directions

- Adults and children 2 years of age and older: Brush teeth thoroughly, preferably after each meal or at least twice a day, or as directed by a dentist or doctor.
- Children 2 to 6 years of age: Instruct children under 6 years of age in good brushing and rinsing habits (to minimize swallowing). Supervise children as necessary until capable of using without supervision.
- Children under 2 years of age: Consult a dentist or doctor.

Inactive Ingredients

Sorbitol, Hydrated Silica, Glycerin, Water, Sodium Lauryl Sulfate, Flavor, Titanium Dioxide, Xanthan Gum, Sodium Benzoate, Benzoic Acid, Sodium Saccharin, Zinc Chloride, D&C Yellow #10 and FD&C Blue #1

Questions or comments

1-800-492-7040

SmartMouth™ is a trademark of
and distributed by:
Triumph
Pharmaceuticals Inc.
St. Louis, Missouri 63132
Made in USA ©2011

PRINCIPAL DISPLAY PANEL - 170 g Tube Label

smart
mouth™

Anti-Cavity

Toothpaste

with Fluoride

Zn^+2

SMART-ZINC™
TECHNOLOGY

Protect • Clean • Repair

Remineralizes Weakened Enamel

Removes Dental Plaque

Dentist Recommended

MILD MINT • NET WT. 6 OZ (170g)